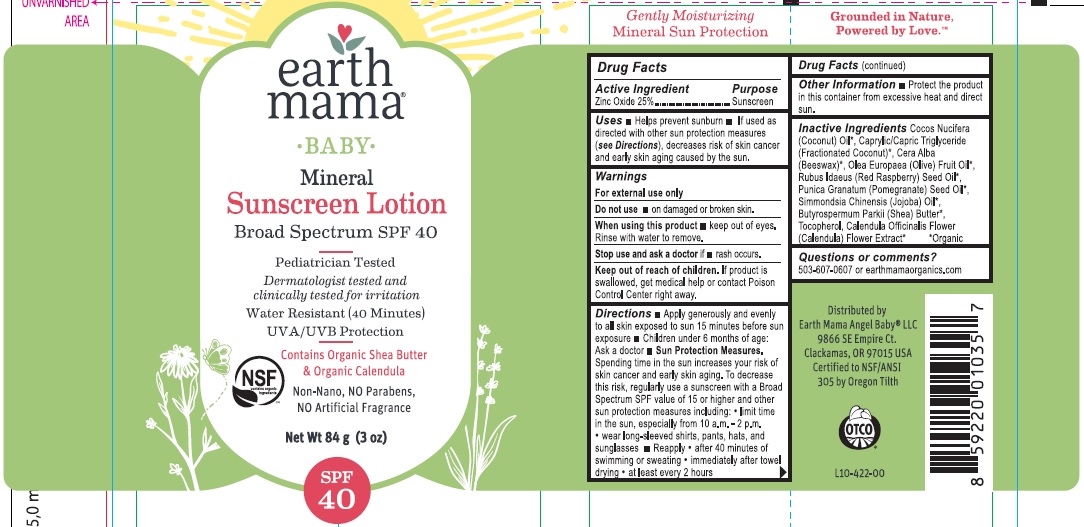 DRUG LABEL: SUNSCREEN
NDC: 62932-170 | Form: OINTMENT
Manufacturer: Private Label Select Ltd CO
Category: otc | Type: HUMAN OTC DRUG LABEL
Date: 20181108

ACTIVE INGREDIENTS: ZINC OXIDE 25 g/100 g
INACTIVE INGREDIENTS: COCONUT OIL; CAPRYLIC/CAPRIC/LAURIC TRIGLYCERIDE; YELLOW WAX; OLEA EUROPAEA FRUIT VOLATILE OIL; RASPBERRY SEED OIL; SHEA BUTTER; PUNICA GRANATUM SEED OIL; SIMMONDSIA CHINENSIS SEED WAX; TOCOPHEROL; CALENDULA OFFICINALIS FLOWER

earth mama Baby Mineral Sunscreen SPF40 Lotion